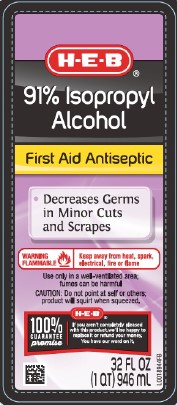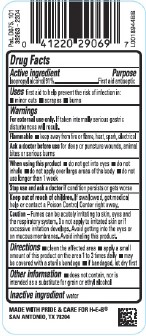 DRUG LABEL: Isopropyl Alcohol
NDC: 37808-804 | Form: LIQUID
Manufacturer: H E B
Category: otc | Type: HUMAN OTC DRUG LABEL
Date: 20260224

ACTIVE INGREDIENTS: ISOPROPYL ALCOHOL 91 mL/100 mL
INACTIVE INGREDIENTS: WATER

HEB 804.003/804AA
91% Isopropyl Alcohol

Active ingredient

Isopropyl alcohol 91%

purpose

First aid antiseptic

Use

First aid to help prevent the rist of infection in:

- minor cuts
- scrapes
- burns

Warnings

For external use only. If taken internally serious gastric disturbances will result.

Flammable - Keep away from fire or flame, heat, spark, electrical

Ask a doctor before use

for deep or puncture wounds, animal bites or serious burns

When using this product

- do not get into eyes
- do not inhale
- do not apply over large areas of the body
- do not use longer than 1 week

Stop use and ask a doctor if

condition persists or gets worse

Keep out of reach of children.

If swallowed, get medical help or contact a Poison Control Center right away.

Caution

Fumes can be acutely irritating to skin, eyes and respiratory system. Do not apply to irritated skin or if excessive irritation develops. Avoid getting into the eyes or on mucous membranes. Avoid inhaling this product.

Directions

- clean the affected area
- apply a small amount of this product on the area 1 to 3 times daily
- may be covered with a sterile bandage
- if bandaged, let dry first

other information

- does not contain, nor is intended as a substitute for grain or ethyl alcohol

Inactive ingredient

water

Adverse Reaction

MADE WITH PRIDE AND CARE FOR H-E-B

SAN ANTONIO, TX 78204

Pat. D675, 101

principal display panel

H-E-B®

91% Isopropyl Alcohol

First Aid Antiseptic

- Decreases Germs in Minor Cuts and Scrapes

WARNING FLAMMABLE - Keep away from heat, spark, electrical, fire or flame

Use only in a well-ventilated area: fumes can be harmful

CAUTON: Do not point at self or others; product will squirt when squeezed.

H-E-B®

100% Guarantee promise

If you aren't completely pleased with this product, we'll be happy to replace it or refund your money.

You have our word on it.

32 FL OZ (1 QT) 946 mL